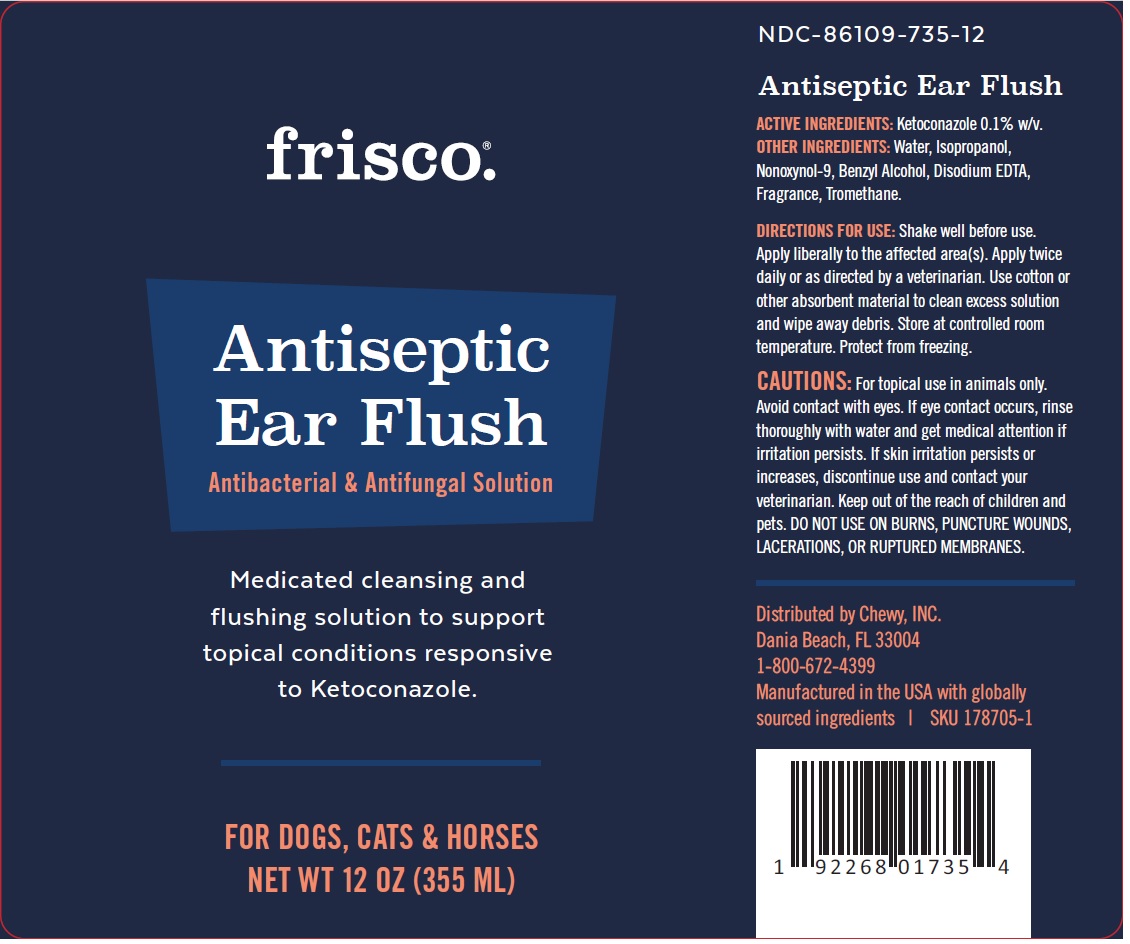 DRUG LABEL: Frisco Antiseptic Ear Flush
NDC: 86109-735 | Form: LIQUID
Manufacturer: Chewy, Inc.
Category: animal | Type: OTC ANIMAL DRUG LABEL
Date: 20201127

ACTIVE INGREDIENTS: KETOCONAZOLE 1 mg/1 mL
INACTIVE INGREDIENTS: WATER; ISOPROPYL ALCOHOL; NONOXYNOL-9; BENZYL ALCOHOL; EDETATE DISODIUM ANHYDROUS; TROMETHAMINE

frisco®. Antiseptic Ear Flush

ACTIVE INGREDIENTS:

Ketoconazole 0.1% w/v.

PURPOSE

Antibacterial & Antifungal Solution

INDICATIONS AND USAGE

Medicated cleansing and flushing solution to support topical conditions responsive to Ketoconazole.

CAUTIONS:

For topical use in animals only. Avoid contact with eyes. If eye contact occurs, rinse thoroughly with water and get medical attention if irritation persists. If skin irritation persists or increases, discontinue use and contact your veterinarian. DO NOT USE ON BURNS, PUNCTURE WOUNDS, LACERATIONS, OR RUPTURED MEMBRANES.

KEEP OUT OF REACH OF CHILDREN

Keep out of the reach of children and pets.

DIRECTIONS FOR USE:

Shake well before use. Apply liberally to the affected area(s). Apply twice daily or as directed by a veterinarian. Use cotton or other absorbent material to clean excess solution and wipe away debris. Store at controlled room temperature. Protect from freezing.

OTHER INGREDIENTS:

Water, Isopropanol, Nonoxynol-9, Benzyl Alcohol, Disodium EDTA, Fragrance, Tromethane.

FOR DOGS, CATS & HORSES

Distributed by Chewy, INC.
Dania Beach, FL 33004
1-800-672-4399

Manufactured in the USA with globally sourced ingredients | SKU 178705-1